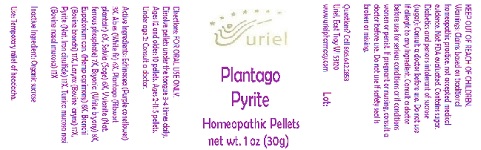 DRUG LABEL: Plantago Pyrite
NDC: 48951-8037 | Form: PELLET
Manufacturer: Uriel Pharmacy Inc.
Category: homeopathic | Type: HUMAN OTC DRUG LABEL
Date: 20180606

ACTIVE INGREDIENTS: ECHINACEA, UNSPECIFIED 3 [hp_X]/1 1; PICEA ABIES LEAF 6 [hp_X]/1 1; PLANTAGO MAJOR LEAF 6 [hp_X]/1 1; SAGE 6 [hp_X]/1 1; FERROSOFERRIC PHOSPHATE 7 [hp_X]/1 1; BRYONIA ALBA ROOT 8 [hp_X]/1 1; EUPATORIUM CANNABINUM FLOWERING TOP 8 [hp_X]/1 1; BEEF LUNG 17 [hp_X]/1 1; THYROID, BOVINE 17 [hp_X]/1 1; FERROUS DISULFIDE 17 [hp_X]/1 1; BOS TAURUS NASAL MUCOSA 17 [hp_X]/1 1
INACTIVE INGREDIENTS: SUCROSE

Plantago Pyrite

INDICATIONS AND USAGE

Directions: FOR ORAL USE ONLY.

DOSAGE AND ADMINISTRATION

Dissolve pellets under the tongue 3-4 times daily. Ages 12 and older: 10 pellets. Ages 2-11: 5 pellets. Under age 2: Consult a doctor.

ACTIVE INGREDIENT

Active Ingredients: Echinacea (Purple coneflower) 3X, Abies (White fir) 6X, Plantago (Ribwort plantain) 6X, Salvia (Sage) 6X, Vivianite (Nat. ferrous phosphate) 7X, Bryonia (White bryony) 8X, Eupatorium can. (Hemp agrimony) 8X, Bronchi (Bovine bronchi) 17X, Larynx (Bovine larynx) 17X, Pyrite (Nat. Iron disulfide) 17X, Tunica mucosa nasi (Bovine nasal mucosa) 17X

Inactive Ingredients: Sucrose, Lactose

PURPOSE

Use: Temporary relief of cough.

KEEP OUT OF REACH OF CHILDREN.

WARNINGS

Warnings: Claims based on traditional homeopathic practice, not accepted medical evidence. Not FDA evaluated. Contains sugar. Diabetics and persons intolerant of sucrose (sugar): Consult a doctor before use. Do not use if allergic to any ingredient. Consult a doctor before use for serious conditions or if conditions worsen or persist. If pregnant or nursing, consult a doctor before use. Do not use if safety seal is broken or missing.

QUESTIONS

Questions? Call 866.642.2858 Uriel, East Troy WI 53120 www.urielpharmacy.com